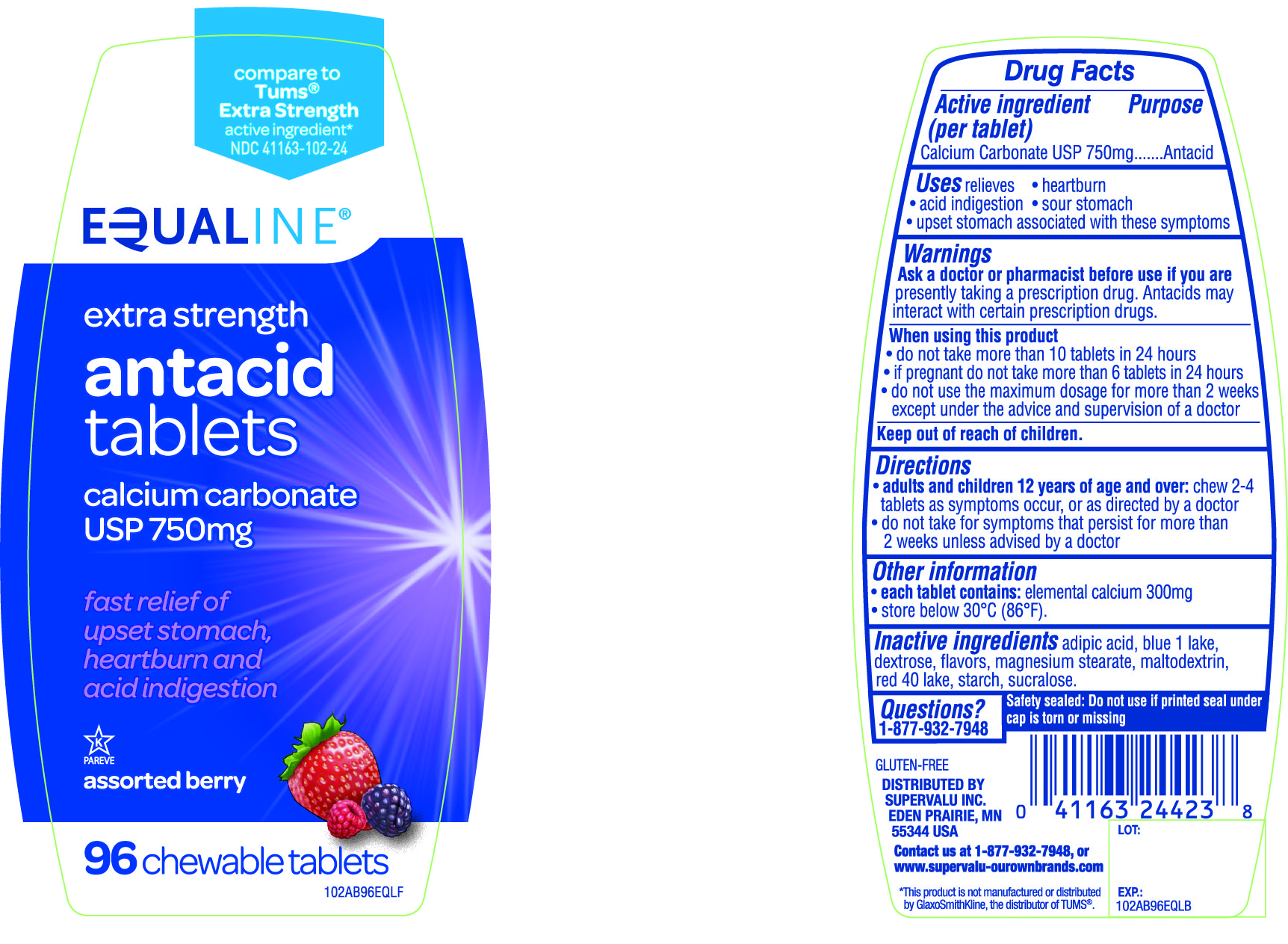 DRUG LABEL: EQUALINE extra strength antacid
NDC: 41163-102 | Form: TABLET, CHEWABLE
Manufacturer: SUPERVALU INC
Category: otc | Type: HUMAN OTC DRUG LABEL
Date: 20171227

ACTIVE INGREDIENTS: CALCIUM CARBONATE 750 mg/1 1
INACTIVE INGREDIENTS: ADIPIC ACID; DEXTROSE; FD&C BLUE NO. 1; FD&C RED NO. 40; MAGNESIUM STEARATE; MALTODEXTRIN; STARCH, CORN; SUCRALOSE

EQUALINE extra strength antacid tablets calcium carbonate 750mg assorted berry 96 chewable tablets

Active ingredient (per tablet)

Calcium Carbonate USP 750mg

Purpose

Antacid

Uses

relieves

• heartburn

• acid indigestion

• sour stomach

• upset stomach associated with these symptoms

Warnings

Ask a doctor or pharmacist before use if you are presently taking a prescription drug. Antacids may interact with certain prescription drugs.

When using this product

- do not take more than 10 tablets in 24 hours
- if pregnant do not take more than 6 tablets in 24 hours
- do not use the maximum dosage for more than 2 weeks except under the advice and supervision of a doctor

Directions

- adults and children 12 years of age and over: chew 2-4 tablets as symptoms occur ,or as directed by a doctor
- do not take for symptoms that persist for more than 2 weeks unless advised by a doctor

Other Information

• each tablet contains: elemental calcium 300mg

• Store below 30°C (86°F).

Inactive ingredients

adipic acid, blue 1 lake, dextrose, flavors, magnesium stearate, maltodextrin, red 40 lake, starch, sucralose.

Questions?

1-877-932-7948

Safety sealed: Do not use if printed seal under cap is torn or missing

Package/Label Principal Display Panel

Compare to Tums® Extra Strength active ingredient*

NDC 41163-102-24

EQUALINE®

extra strength

antacid tablets

calcium carbonate USP 750 mg

fast relief of

upset stomach,

heartburn and

acid indigestion

assorted berry

96 chewable tablets

GLUTEN- FREE

DISTRIBUTED BY

SUPERVALU INC.

EDEN PRAIRIE, MN

55344 USA

Contact us at 1-877-932-7948, or www.supervalu-ourownbrands.com

*This product is not manufactured or distributed by GlaxoSmithKline, the distributor of TUMS®.